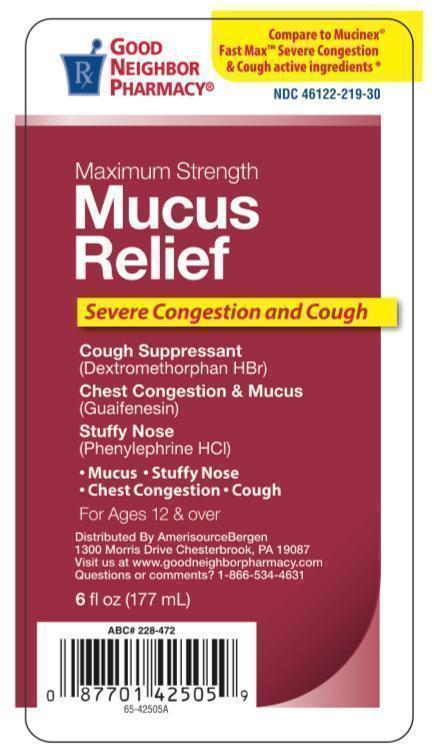 DRUG LABEL: Mucus Relief Severe Congestion and Cough
NDC: 46122-219 | Form: LIQUID
Manufacturer: Good Neighbor Pharmacy
Category: otc | Type: HUMAN OTC DRUG LABEL
Date: 20131104

ACTIVE INGREDIENTS: GUAIFENESIN 400 mg/20 mL; DEXTROMETHORPHAN HYDROBROMIDE 20 mg/20 mL; PHENYLEPHRINE HYDROCHLORIDE 10 mg/20 mL
INACTIVE INGREDIENTS: GLYCERIN; XANTHAN GUM; WATER; DISODIUM EDTA-COPPER; PROPYL GALLATE; SODIUM BENZOATE; SUCRALOSE; SORBITOL; SODIUM CITRATE; FD&C RED NO. 40; FD&C BLUE NO. 1; PROPYLENE GLYCOL; CITRIC ACID ACETATE

Drug Facts

Dextromethorphan HBr 20mg

Guaifenesin 400 mg

Phenylephrine HCl 10mg

Purpose

Dextromethorphan............................Cough suppressant

Guaifenesin................................Expectorant

Phenylephrine HCL..........................Nasal Decongestant

Uses

temporarily relieves cough due to minor throat and bronchial irritation as may occur with the common cold or inhaled irritants the intensity of coughing, the impulse to cough to help you get to sleep, helps loosen phlegm (mucus) and thin bronchial secretions to rid the bronchial passageways of bothersome mucus and make coughs more productive

warnings

for children under 12 years of age

Do not use

if you are now taking a prescription monoamine oxidase inhibitor (MAOI) (certain drugs for depression, psychiatric, or emotional conditions, or Parkinson's disease), or for 2 weeks after stopping the MAOI drug. If you do not know if your prescription drug contains an MAOI, ask a doctor or pharmacist before taking this product.

Ask a doctor before use if you have

persistent or chronic cough such as occurs with smoking, astha, chrinic bronchitis or emphysema

cough that occurs with too much phlegm (mucus)

when using this product

do not use more than directed

stop use and ask a doctor if

cough lasts more than 7 days, comes back, or occurs with fever, rash or persistent headache. These could be signs of a serious condition.

If pregnant or breast feeding

ask a health professional before use.

Keep out of reach of children

In case of overdose, get medical help or contact a Poison Control Center 1-800-222-1222 immediately. Quick medical attention is critical for adults as well as for children even if you do not notice any signs or symptoms.

Directions

do not exceed recommended dosage

use dosage cup provided

do not take more than 6 doses in a 24 hour period

do not use dosing cup with other products

dose as follows or as directed by a doctor mL=milliliter

children under 12 years-do not use

adults and children 12 years and older-20mL every 4 hours

Other information

each 20mL contains potassium 6mg, sodium 13mg

store at room temperature

do not refrigerate

Inactive ingredients

citric acid, dextrose, flavors, glycerin, methyl paraben, potassium sorbate, propylene glycol, propyl paraben, purified water, red 33, red 40, saccharin sodium, sodium hydroxide, sucralose, xanthan gum

Principal Display Panel

Maximum Strength

Mucus Relief

Severe Congestion and Cough

Cought Suppressant

(Dextromethorphan HBr)

Chest Congestion and Mucus

(Guaifenesin)

Stuffy Nose

(Phenylephrine HCl)

Mucus, Stuffy Nose, Chest Congestion, Cough

For Ages 12 and over

Distrubted By AmerisourceBergen

1300 Morris Drive Chesterbrook PA 19087

Visit us at www.goodneighborpharmacy.com

Questions or comments? 1 866 534 4631

6 fl oz 177 mL